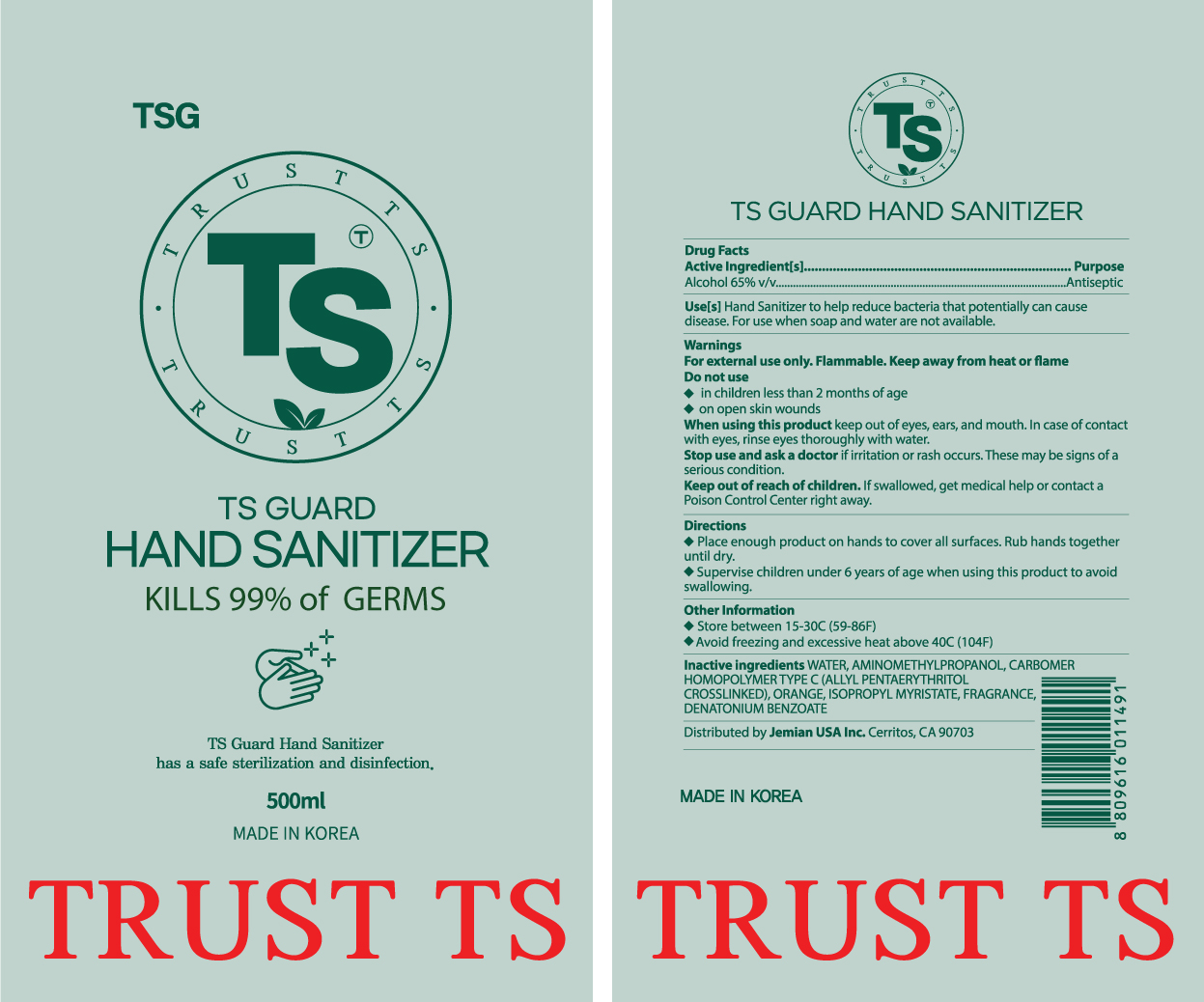 DRUG LABEL: TS Guard
NDC: 73917-0202 | Form: GEL
Manufacturer: Jemian USA Inc.
Category: otc | Type: HUMAN OTC DRUG LABEL
Date: 20200526

ACTIVE INGREDIENTS: ALCOHOL 65 mL/100 mL
INACTIVE INGREDIENTS: DENATONIUM BENZOATE; AMINOMETHYLPROPANOL (PERFLUORO-C6-C12 ETHYL)PHOSPHATE; CARBOMER HOMOPOLYMER TYPE C (ALLYL PENTAERYTHRITOL CROSSLINKED); ORANGE; ISOPROPYL MYRISTATE; FRAGRANCE LAVENDER & CHIA F-153480

TS Guard Hand Sanitizer

Active Ingredients:

Alcohol 65%

PURPOSE

Antiseptic

Warnings

For external use only : hands

Flammable.: keep away from fire or flame.

When Using This Product

Keep out of eyes, In case of contact with eyes, rinse with water

When Using This Product

Keep out of eyes, In case of contact with eyes, rinse with water

Stop using this product

irritation and redness develops and persists.

Keep out of reach of children.

If swallowed, get medical help promptly and Poison Control

INDICATIONS AND USAGE

Kills 99% of germs!

Inactive Ingedients

water, aminomethylpropanol, carbomer homopolymer type C (allyl pentearythritol crosslinked), orange, isopropyl myristate, fragnance, denatonium benzoate

Direction

Wet hands throughly with product and allow to dry without wiping

Other Information

do not store above 105 F

may discolor some fabric

PRINCIPAL DISPLAY PANEL

500ml 73917-0201-1

100ml 73917-0201-2